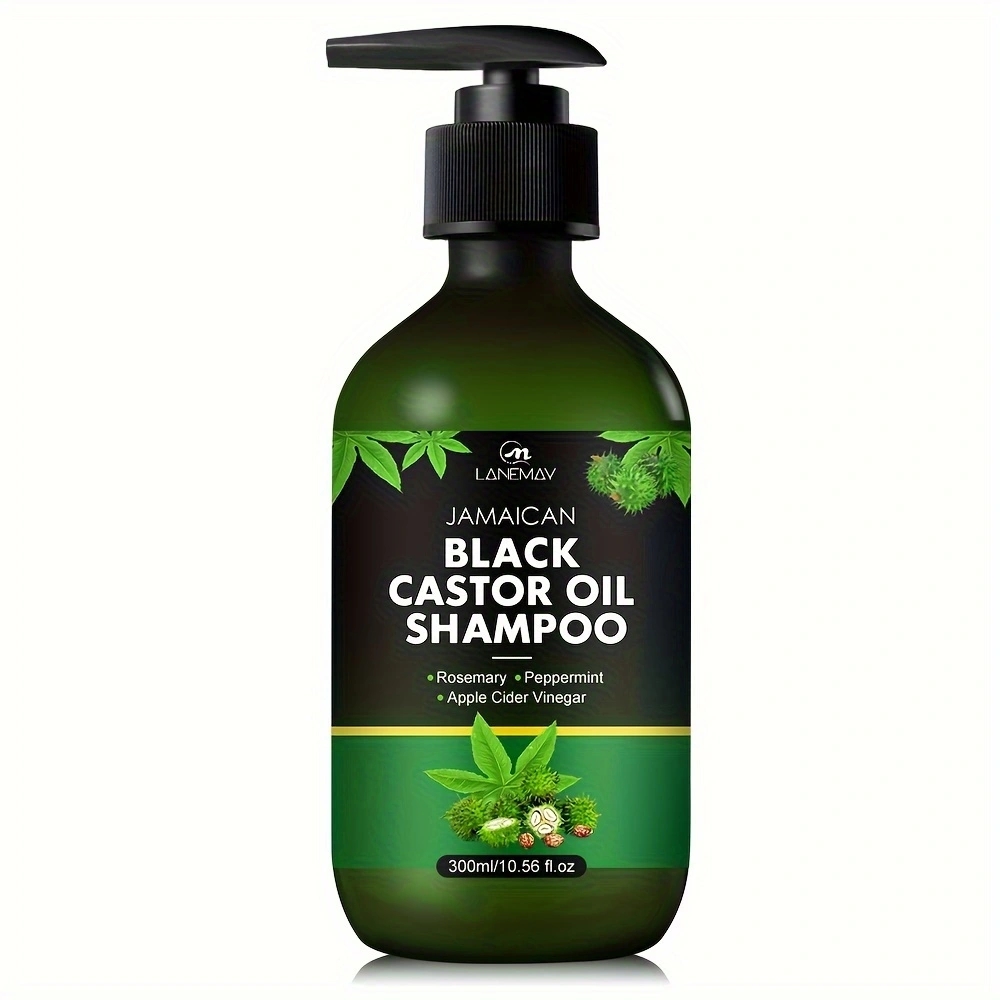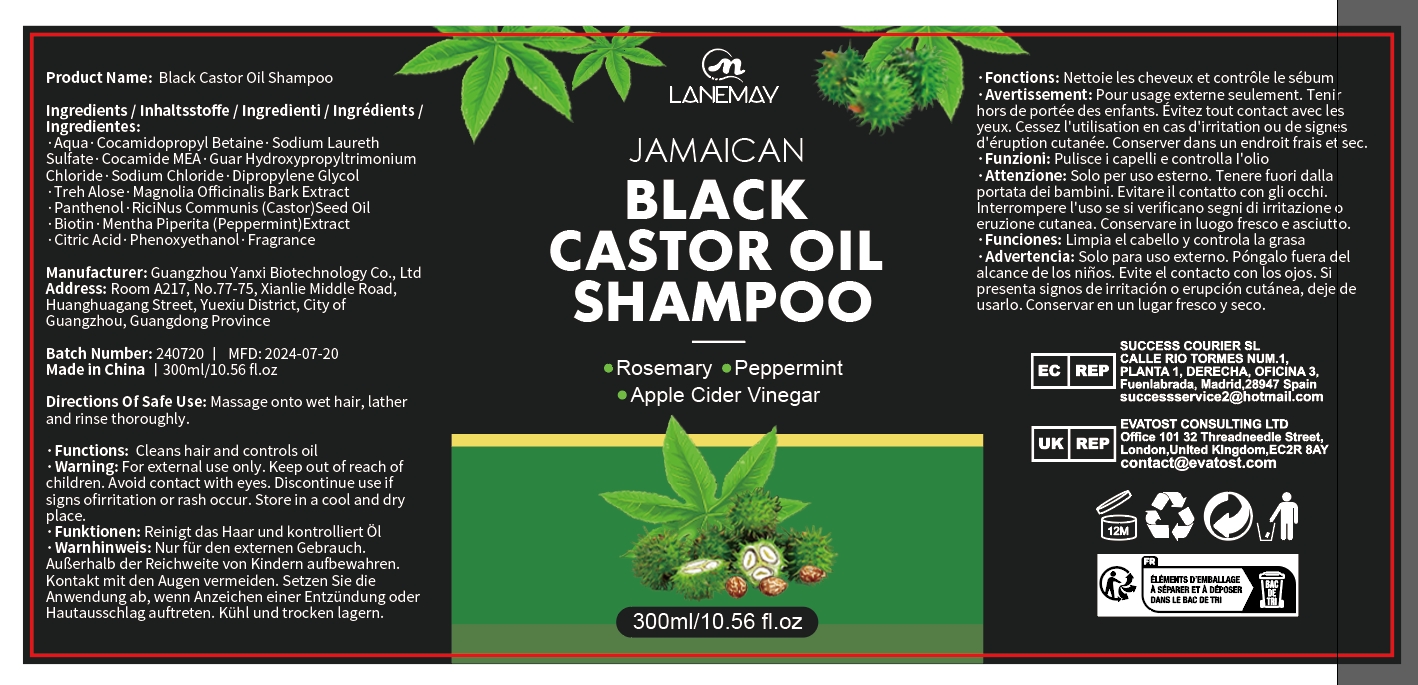 DRUG LABEL: Black Castor OilShampoo
NDC: 84025-166 | Form: SHAMPOO
Manufacturer: Guangzhou Yanxi Biotechnology Co.. Ltd
Category: otc | Type: HUMAN OTC DRUG LABEL
Date: 20240826

ACTIVE INGREDIENTS: DIPROPYLENE GLYCOL 3 mg/300 mL; COCAMIDOPROPYL BETAINE 5 mg/300 mL
INACTIVE INGREDIENTS: WATER

DOSAGE AND ADMINISTRATION

Shampoo for nourishing and caring scalp and hair

WARNINGS

keep out of chidlren

INACTIVE INGREDIENT

AQUA

INDICATIONS AND USAGE

For daily scalp and hair care

keep out of children

PURPOSE

Effectively maintains healthy scalp and smooth hair